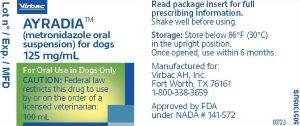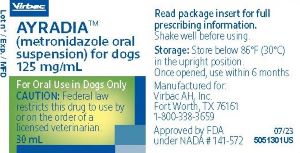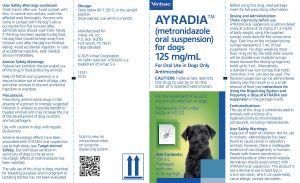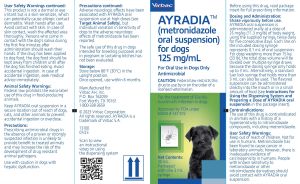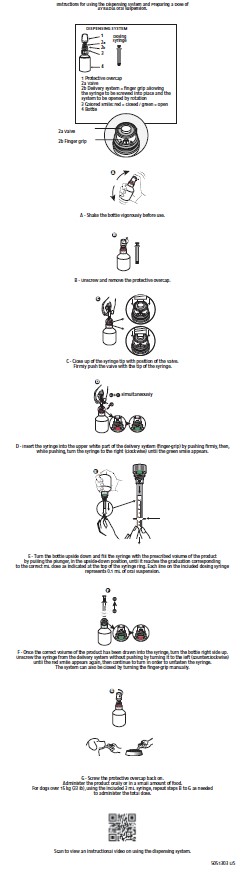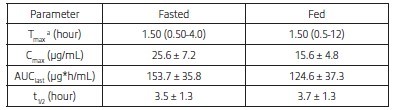 DRUG LABEL: AYRADIA
NDC: 51311-034 | Form: SOLUTION
Manufacturer: Virbac AH Inc
Category: animal | Type: PRESCRIPTION ANIMAL DRUG LABEL
Date: 20231026

ACTIVE INGREDIENTS: METRONIDAZOLE 125 mg/1 mL

AYRADIA (metronidazole oral suspension) for dogs

GENERAL PRECAUTIONS

125 mg/mL

For Oral Use in Dogs Only
Antimicrobial

CAUTION
Federal law restricts this drug to use by or on the order of a licensed veterinarian.

Description

AYRADIA™ (metronidazole oral suspension) for dogs contains metronidazole USP. Metronidazole is a nitroimidazole, in the drug class anti-infectives, with anti-bacterial and anti-protozoal activities. The product is a flavored oily suspension with brown visible particles. The chemical composition of metronidazole is 2-(2-methyl-5-nitroimidazol-1-yl) ethanol. The empirical formula of metronidazole is: C6H9N3O3.

AYRADIA oral suspension contains 125 mg metronidazole/mL in a flavored, medium-chain triglyceride, liquid base.

Indication

AYRADIA oral suspension is indicated for the treatment of Giardia duodenalis infection in dogs.

Dosage and Administration

Shake vigorously before use.
AYRADIA oral suspension is administered orally at a dose of 25 mg/kg (11.3 mg/lb) of body weight, using the supplied syringe, twice daily for five consecutive days. Each line on the included dosing syringe represents 0.1 mL of oral suspension. For dogs weighing more than 15 kg (33 lb), the total dose volume will be divided over multiple syringe draws because the dosing syringe only holds up to 3 mL. Alternatively, a standard luer lock syringe that holds more than 3 mL can also be used. The flavored suspension can be administered directly into the mouth or in a small amount of food (see Instructions for Using the Dispensing System and Preparing a Dose of AYRADIA oral suspension on reverse side).

Contraindications

The use of this drug is contraindicated in animals with a history of a hypersensitivity to nitroimidazole compounds, including metronidazole.

Warnings

User Safety Warnings
Keep out of reach of children. Not for use in humans. Metronidazole has been found to cause cancer in laboratory animals; however, there is inadequate evidence of carcinogenicity in humans. People with known sensitivity to metronidazole or other nitroimidazole derivatives should avoid contact with AYRADIA oral suspension. This product is not a dermal or eye irritant but is a skin sensitizer which can potentially cause allergic contact dermatitis. Wash hands after use. Avoid contact with skin. In case of skin contact, wash the affected area thoroughly. Persons who come in contact with the dog’s saliva during the first five minutes after administration should wash their hands. If the drug has been applied to dog food, the dog food should be kept away from children until after the dog has finished eating. Avoid accidental ingestion. In case of accidental ingestion, seek medical advice immediately.

Animal Safety Warnings
Federal law prohibits the extra-label use of this drug in food-producing animals.

Keep AYRADIA oral suspension in a secure location out of reach of dogs, cats, and other animals to prevent accidental ingestion or overdose.

Precautions

Prescribing antimicrobial drugs in the absence of a proven or strongly suspected infection is unlikely to provide benefit to treated animals and may increase the risk of the development of drug resistant animal pathogens.

Use with caution in dogs with hepatic dysfunction.

Adverse neurologic effects have been associated with AYRADIA oral suspension use at high doses (see Target Animal Safety), but individual variation in sensitivity of dogs to the adverse neurologic effects of metronidazole has been reported.

The safe use of this drug in dogs intended for breeding purposes and in pregnant or lactating bitches has not been evaluated.

Adverse Reactions

In a clinical field effectiveness and safety study, 120 dogs were treated with AYRADIA oral suspension and 60 dogs were treated with a vehicle control. The most frequently reported adverse reactions were diarrhea (6.7% treated, 5% vehicle) and vomiting (4.2% treated, 3.3% vehicle). One dog treated with AYRADIA oral suspension was reported to have hyperactivity while being treated.

The safety of AYRADIA oral suspension was also evaluated in a masked, active-controlled, multi-site field study, to evaluate the effectiveness of AYRADIA oral suspension for the treatment of Giardia spp. in dogs. Enrollment included 180 client-owned dogs diagnosed with Giardia spp. infection; 91 dogs were treated with AYRADIA oral suspension at 25 mg/kg twice daily for 5 consecutive days and 89 were treated with an active control. The dogs were 7.8 weeks to 13.4 years old, various pure or mixed breeds, and intact or neutered male dogs or intact or spayed female dogs. The most frequently reported adverse reactions in dogs treated with AYRADIA oral suspension were vomiting (14.3%) and diarrhea (3.3%). Other less frequently reported (<1.2%) adverse reactions included hypersalivation, abdominal pain, polydipsia and polyuria, anorexia, otitis externa, and lethargy.

Contact Information
To report suspected adverse drug events, for technical assistance or to obtain a copy of the Safety Data Sheet (SDS), contact Virbac AH, Inc. at 1-800-338-3659 or us.virbac.com. For additional information about adverse drug experience reporting for animal drugs, contact FDA at 1-888-FDA-VETS or http://www.fda.gov/reportanimalae

Clinical Pharmacology

Mechanism of Action
Metronidazole is a nitroimidazole compound known to exert antiprotozoal and antibacterial activity. Metronidazole has antiprotozoal activity against Giardia duodenalis. The mechanism of action for its antiprotozoal activity is not well understood but it acts primarily against the trophozoite forms of the parasites resulting in a decrease in cyst shedding. Metronidazole is reduced as it enters the susceptible target cell where it interacts with bacterial or protozoal DNA, causing a loss of helical structure and strand breakage in the DNA. This breakage leads to the inhibition of nucleic acid synthesis and therefore causes death of the bacterial or protozoal cell.

Pharmacokinetics

Metronidazole is a moderately lipophilic, low molecular weight, weak base that penetrates cell membranes and is well absorbed systemically.

The pharmacokinetics of AYRADIA oral suspension were evaluated in a cross-over study in 6 male and 6 female Beagle dogs receiving a single oral dose of 25 mg/kg metronidazole in the fed or fasted state. Following overnight fasting, half the dogs were fed a meal of dry dog food 15 minutes before dosing and the other dogs continued to be fasted until 4 hours post metronidazole administration. Blood samples were collected prior to dosing and at 0.25, 0.5, 1, 1.5, 2, 4, 6, 8, 12, 24, 30, and 48 hours post- dosing. Plasma concentrations of metronidazole were measured using a liquid chromatography with mass spectrometry detection method.

Table 1. Mean (Standard Deviation) Pharmacokinetic Parameters for Plasma Metronidazole.

aMedian and Range
Tmax = time to maximum plasma concentration
Cmax = maximum plasma concentration
AUClast = area under the curve from the time of dosing to the last quantifiable plasma concentration
t1/2 = elimination half-life

The maximum plasma concentration (Cmax) and area under the curve from the time of dosing to the last quantifiable plasma concentration (AUClast) for metronidazole were 39 and 20% lower, respectively, in the fed state, as compared to the fasted state. In a separate cross-over study, following oral and intravenous administration of 25 mg/kg metronidazole to twelve Beagle dogs, the mean absolute bioavailability, clearance (CL), and volume of distribution (Vd) of metronidazole oral suspension were 97.6%,
118 mL/hour/kg, and 628 mL/kg, respectively.

Effectiveness
The effectiveness of AYRADIA oral suspension was demonstrated in one dose confirmation laboratory study and one field effectiveness and safety study. AYRADIA oral suspension was administered at a dose of 25 mg/kg twice daily for five consecutive days in both studies.

The dose confirmation laboratory study was a parallel, masked, negative (sterile water) controlled study to evaluate effectiveness in naturally occurring Giardia duodenalis infection in dogs based on post-treatment intestinal trophozoite counts. The study included 13 healthy beagle dogs naturally infected with Giardia with pre-treatment cyst counts of ≥ 750 cysts/gram feces. The dogs were between 8.1 and 10.9 months of age and weighed between 9.8 and 14.6 kg (21.6 and 32.2 lbs). A statistically significant difference in trophozoite counts on Day 8, four days after the last dose, was detected in the AYRADIA-treated group as compared to the control group (geometric mean counts in the control group = 339,617 versus 1,056 in the treated group; p = 0.0026). The relative difference between the AYRADIA-treated group and the control group was calculated to be 99.7%.

The field effectiveness and safety study was a double-masked, vehicle-controlled, randomized, multi-center study conducted at veterinary clinics and shelters or non-breed-specific rescue groups to evaluate the effectiveness of AYRADIA oral suspension to treat dogs naturally infected with Giardia duodenalis. Effectiveness was evaluated in 120 of the 180 dogs enrolled (80 in the AYRADIA oral suspension group and 40 in the control group). Dogs ranged in age from 5 weeks to 15.2 years old, weighed 2.0 and 37.2 kg (4.4 and 81.8 lbs), were of various pure or mixed breeds, and included intact, non-pregnant and non-lactating, or spayed females, and intact or neutered males.

Observations included baseline physical examination, body weight, hematology, serum chemistry, and urinalysis before and after treatment. In addition, three daily fecal samples before and three daily fecal after treatment were obtained for immunofluorescence assay (IFA) cyst counts. Safety was monitored during the study by documentation of adverse events (see Adverse Reactions).

The difference between AYRADIA oral suspension and the vehicle control in terms of post-treatment cyst counts was significantly different (p<0.001) and in favor of the AYRADIA-treated dogs. Additionally, there was a 99.9% percent reduction in cyst counts between baseline and post-treatment in the AYRADIA-treated group. Based on these results, AYRADIA oral suspension was demonstrated to be effective for the treatment of Giardia duodenalis in naturally infected dogs.

Target Animal Safety
In a laboratory safety study, 12-week old, healthy, Beagle puppies (4/sex/group) were administered AYRADIA oral suspension at 0X, 1X, 2X and 3X the therapeutic dose (25 mg/kg twice per day) for 15 days (3X the treatment duration) and at 5X the therapeutic dose for 5 days (the treatment duration). AYRADIA oral suspension at 5X the therapeutic dose was associated with self-limiting episodes of diarrhea and erythema of the ears. No other clinically relevant observations were noted during the study.

In a four-dog laboratory tolerance study, two dogs, approximately four months old, received an investigational metronidazole oral suspension formulation (160 mg/mL) at 500 mg/kg/day (10X the intended daily dose) for 7 days, and two dogs (one 12 months old and one 21 months old) received a commercially-available metronidazole tablet at 250 mg/kg/day (5X the intended daily dose) for 7 days. No abnormal clinical signs were observed in dogs treated at 250 mg/kg/day with the metronidazole tablet. The two dogs that received the metronidazole oral suspension at 500 mg/kg/day exhibited severe neurologic signs by Days 7 and 8, respectively. Ataxia and lack of ocular reflexes were observed in both dogs. Additional adverse signs in one of the dogs included lateral movements of head and eyes, recumbency, tremors, and mydriasis. The dogs recovered after cessation of metronidazole administration and treatment with repeated doses of diazepam and furosemide. Both dogs recovered fully within approximately 24 hours.

Storage Conditions

Store below 86°F (30°C) in the upright position.
Once opened, use within 6 months.

How Supplied

AYRADIA™ (metronidazole oral suspension) for dogs is supplied in bottle sizes of 30 mL and 100 mL oral suspension.
Bottles come pre-assembled with a dispensing system and a 3 mL syringe is included in each carton.

Approved by FDA under NADA # 141-572

Manufactured for:
Virbac AH, Inc.
P.O. Box 162059
Fort Worth, TX 76161
1-800-338-3659
us.virbac.com

Rev. 07/2023

© 2023 Virbac Corporation. All Rights Reserved.
AYRADIA is a trademark of Virbac S.A.